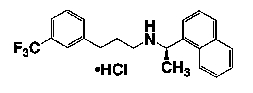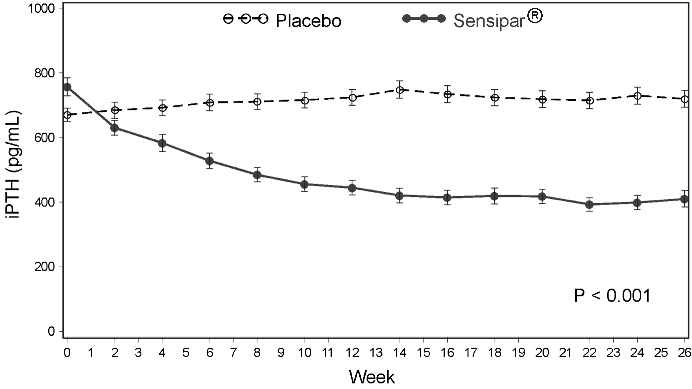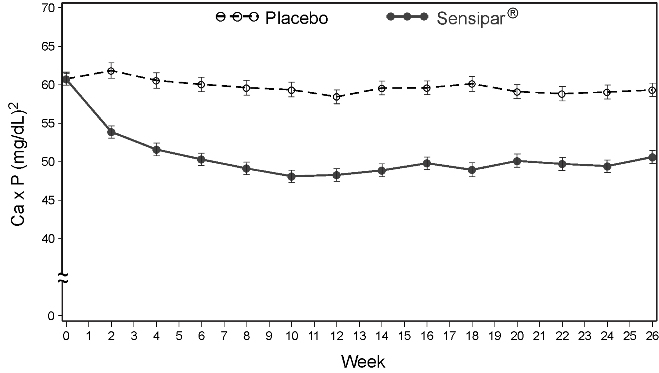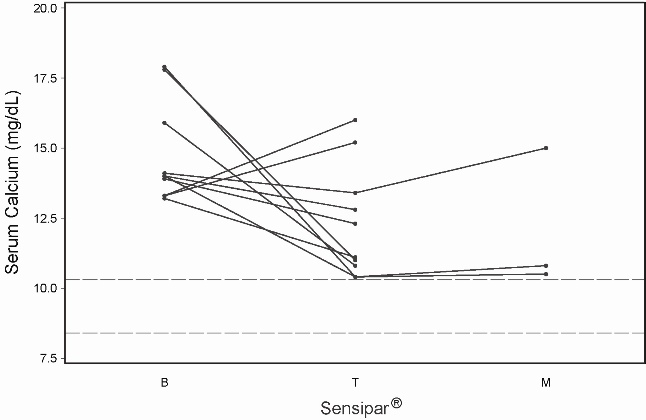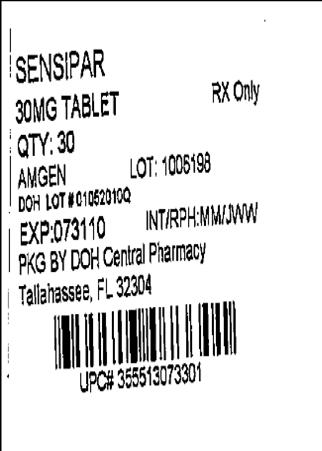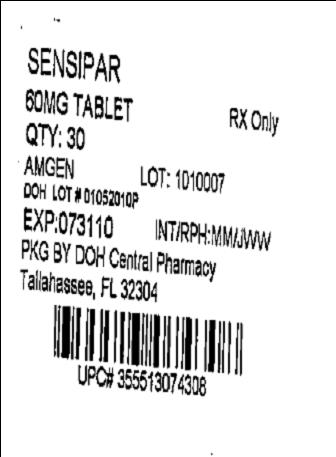 DRUG LABEL: Sensipar
NDC: 53808-0577 | Form: TABLET, COATED
Manufacturer: State of Florida DOH Central Pharmacy
Category: prescription | Type: HUMAN PRESCRIPTION DRUG LABEL
Date: 20100608

ACTIVE INGREDIENTS: CINACALCET HYDROCHLORIDE 30 mg/1 1
INACTIVE INGREDIENTS: CARNAUBA WAX; CELLULOSE, MICROCRYSTALLINE; CROSPOVIDONE; MAGNESIUM STEARATE; POVIDONE; STARCH, CORN; SILICON DIOXIDE

Sensipar® (cinacalcet) Tablets

Description

Sensipar® (cinacalcet) is a calcimimetic agent that increases the sensitivity of the calcium-sensing receptor to activation by extracellular calcium. Its empirical formula is C22H22F3N•HCl with a molecular weight of 393.9 g/mol (hydrochloride salt) and 357.4 g/mol (free base). It has one chiral center having an R-absolute configuration. The R-enantiomer is the more potent enantiomer and has been shown to be responsible for pharmacodynamic activity.

Cinacalcet is a white to off-white, crystalline solid that is soluble in methanol or 95% ethanol and slightly soluble in water.

Sensipar® tablets are formulated as light-green, film-coated, oval-shaped tablets for oral administration in strengths of 30 mg, 60 mg, and 90 mg of cinacalcet as the free base equivalent (33 mg, 66 mg, and 99 mg as the hydrochloride salt, respectively).

Cinacalcet is described chemically as N-[1-(R)-(-)-(1-naphthyl)ethyl]-3-[3-(trifluoromethyl)phenyl]-1-aminopropane hydrochloride and has the following structural formula:

Inactive Ingredients: Sensipar® tablets are comprised of the active ingredient, and the following inactive ingredients: pre-gelatinized starch, microcrystalline cellulose, povidone, crospovidone, colloidal silicon dioxide, and magnesium stearate. Tablets are coated with color (Opadry® II green), clear film-coat (Opadry® clear) and carnauba wax.

CLINICAL PHARMACOLOGY

Mechanism of Action

Secondary hyperparathyroidism (HPT) in patients with chronic kidney disease (CKD) is a progressive disease, associated with increases in parathyroid hormone (PTH) levels and derangements in calcium and phosphorus metabolism. Increased PTH stimulates osteoclastic activity resulting in cortical bone resorption and marrow fibrosis. The goals of treatment of secondary hyperparathyroidism are to lower levels of PTH, calcium, and phosphorus in the blood, in order to prevent progressive bone disease and the systemic consequences of disordered mineral metabolism. In CKD patients on dialysis with uncontrolled secondary HPT, reductions in PTH are associated with a favorable impact on bone-specific alkaline phosphatase (BALP), bone turnover and bone fibrosis.

The calcium-sensing receptor on the surface of the chief cell of the parathyroid gland is the principal regulator of PTH secretion. Sensipar® directly lowers PTH levels by increasing the sensitivity of the calcium-sensing receptor to extracellular calcium. The reduction in PTH is associated with a concomitant decrease in serum calcium levels.

Pharmacokinetics

Absorption and Distribution: After oral administration of cinacalcet, maximum plasma concentration (Cmax) is achieved in approximately 2 to 6 hours. A food-effect study in healthy volunteers indicated that the Cmax and area under the curve (AUC(0-inf)) were increased 82% and 68%, respectively, when cinacalcet was administered with a high-fat meal compared to fasting. Cmax and AUC(0-inf) of cinacalcet were increased 65% and 50%, respectively, when cinacalcet was administered with a low-fat meal compared to fasting.

After absorption, cinacalcet concentrations decline in a biphasic fashion with a terminal half-life of 30 to 40 hours. Steady-state drug levels are achieved within 7 days. The mean accumulation ratio is approximately 2 with once-daily oral administration. The median accumulation ratio is approximately 2 to 5 with twice-daily oral administration. The AUC and Cmax of cinacalcet increase proportionally over the dose range of 30 to 180 mg once daily. The pharmacokinetic profile of cinacalcet does not change over time with once-daily dosing of 30 to 180 mg. The volume of distribution is high (approximately 1000 L), indicating extensive distribution. Cinacalcet is approximately 93 to 97% bound to plasma protein(s). The ratio of blood cinacalcet concentration to plasma cinacalcet concentration is 0.80 at a blood cinacalcet concentration of 10 ng/mL.

Metabolism and Excretion: Cinacalcet is metabolized by multiple enzymes, primarily CYP3A4, CYP2D6 and CYP1A2. After administration of a 75 mg radiolabeled dose to healthy volunteers, cinacalcet was rapidly and extensively metabolized via: 1) oxidative N-dealkylation to hydrocinnamic acid and hydroxy-hydrocinnamic acid, which are further metabolized via β-oxidation and glycine conjugation; the oxidative N-dealkylation process also generates metabolites that contain the naphthalene ring; and 2) oxidation of the naphthalene ring on the parent drug to form dihydrodiols, which are further conjugated with glucuronic acid. The plasma concentrations of the major circulating metabolites including the cinnamic acid derivatives and glucuronidated dihydrodiols markedly exceed parent drug concentrations. The hydrocinnamic acid metabolite was shown to be inactive at concentrations up to 10 µM in a cell-based assay measuring calcium-receptor activation. The glucuronide conjugates formed after cinacalcet oxidation were shown to have a potency approximately 0.003 times that of cinacalcet in a cell-based assay measuring a calcimimetic response. Renal excretion of metabolites was the primary route of elimination of radioactivity. Approximately 80% of the dose was recovered in the urine and 15% in the feces.

Special Populations

Hepatic Insufficiency: The disposition of a 50 mg cinacalcet single dose was compared in patients with hepatic impairment and subjects with normal hepatic function. Cinacalcet exposure, AUC(0-inf), was comparable between healthy volunteers and patients with mild hepatic impairment. However, in patients with moderate and severe hepatic impairment (as indicated by the Child-Pugh method), cinacalcet exposures as defined by the AUC(0-inf) were 2.4 and 4.2 times higher, respectively, than that in normals. The mean half-life of cinacalcet is prolonged by 33% and 70% in patients with moderate and severe hepatic impairment, respectively. Protein binding of cinacalcet is not affected by impaired hepatic function. See PRECAUTIONS and DOSAGE AND ADMINISTRATION.

Renal Insufficiency: The pharmacokinetic profile of a 75 mg Sensipar® single dose in patients with mild, moderate, and severe renal insufficiency, and those on hemodialysis or peritoneal dialysis is comparable to that in healthy volunteers.

Geriatric Patients: The pharmacokinetic profile of Sensipar® in geriatric patients (age ≥ 65, n = 12) is similar to that for patients who are < 65 years of age (n = 268).

Pediatric Patients: The pharmacokinetics of Sensipar® have not been studied in patients < 18 years of age.

Drug Interactions

An in vitro study indicates that cinacalcet is a strong inhibitor of CYP2D6, but not of CYP1A2, CYP2C9, CYP2C19, and CYP3A4. In vitro induction studies indicate that cinacalcet is not an inducer of CYP450 enzymes.

Ketoconazole: Cinacalcet AUC(0-inf) and Cmax increased 2.3 and 2.2 times, respectively, when a single 90 mg cinacalcet dose on Day 5 was administered to subjects treated with 200 mg ketoconazole twice daily for 7 days compared to 90 mg cinacalcet given alone (see DOSAGE AND ADMINISTRATION).

Calcium Carbonate: No significant pharmacokinetic interaction was observed when a single dose of 1500 mg calcium carbonate was coadministered with 100 mg cinacalcet.

Pantoprazole: No significant pharmacokinetic interaction was observed when cinacalcet 90 mg was administered to subjects treated with 80 mg pantoprazole daily for 3 days.

Sevelamer HCl: No significant pharmacokinetic interaction was observed when 2400 mg sevelamer HCl was coadministered with 90 mg cinacalcet tablet (subjects subsequently received 2400 mg sevelamer HCl two more times on Day 1 and three more times on Day 2).

Desipramine: The effect of cinacalcet (90 mg) on the pharmacokinetics of desipramine (50 mg) has been studied in healthy subjects who were CYP2D6 extensive metabolizers. The AUC and Cmax of desipramine increased by 3.6 (296.5-446.7%) and 1.75 (157.5-194.9%) fold, respectively, in the presence of cinacalcet. This indicates that cinacalcet is a strong in vivo inhibitor of CYP2D6 and can increase the blood concentrations of drugs metabolized by CYP2D6.

Amitriptyline: Concurrent administration of 25 mg or 100 mg cinacalcet with 50 mg amitriptyline increased amitriptyline exposure and nortriptyline (active metabolite) exposure by approximately 20% in CYP2D6 extensive metabolizers.

Warfarin: R- and S-warfarin pharmacokinetics and warfarin pharmacodynamics were not affected in subjects treated with warfarin 25 mg who received cinacalcet 30 mg twice daily. The lack of effect of cinacalcet on the pharmacokinetics of R- and S-warfarin and the absence of auto-induction upon multiple dosing in patients indicates that cinacalcet is not an inducer of CYP2C9 in humans.

Midazolam: There were no significant differences in the pharmacokinetics of midazolam, a CYP3A4 and CYP3A5 substrate, in subjects receiving 90 mg cinacalcet once daily for 5 days and a single dose of 2 mg midazolam on day 5 as compared to those of subjects receiving 2 mg midazolam alone. This suggests that cinacalcet would not affect the pharmacokinetics of drugs predominantly metabolized by CYP3A4 and CYP3A5.

Pharmacodynamics

Reduction in intact PTH (iPTH) levels correlated with cinacalcet concentrations in CKD patients. The nadir in iPTH level occurs approximately 2 to 6 hours post dose, corresponding with the Cmax of cinacalcet. After steady state is reached, serum calcium concentrations remain constant over the dosing interval in CKD patients.

CLINICAL STUDIES

Secondary Hyperparathyroidism in Patients with Chronic Kidney Disease on Dialysis

Three 6-month, multicenter, randomized, double-blind, placebo-controlled clinical studies of similar design were conducted in CKD patients on dialysis. A total of 665 patients were randomized to Sensipar® and 471 patients to placebo. The mean age of the patients was 54 years, 62% were male, and 52% Caucasian. The average baseline iPTH level by the Nichols intact immunoradiometric assay (IRMA) was 712 pg/mL, with 26% of the patients having a baseline iPTH level > 800 pg/mL. The mean baseline Ca x P ion product was 61 mg^2/dL^2. The average duration of dialysis prior to study enrollment was 67 months. Ninety-six percent of patients were on hemodialysis and 4% peritoneal dialysis. At study entry, 66% of the patients were receiving vitamin D sterols and 93% were receiving phosphate binders. Sensipar® (or placebo) was initiated at a dose of 30 mg once daily and titrated every 3 or 4 weeks to a maximum dose of 180 mg once daily to achieve an iPTH of ≤ 250 pg/mL. The dose was not increased if a patient had any of the following: iPTH < 200 pg/mL, serum calcium < 7.8 mg/dL, or any symptoms of hypocalcemia. If a patient experienced symptoms of hypocalcemia or had a serum calcium < 8.4 mg/dL, calcium supplements and/or calcium-based phosphate binders could be increased. If these measures were insufficient, the vitamin D dose could be increased. Approximately 70% of the Sensipar® patients and 80% of the placebo patients completed the 6-month studies. In the primary efficacy analysis, 40% of Sensipar® patients and 5% of placebo patients achieved an iPTH ≤ 250 pg/mL (p<0.001) (Table 1, Figure 1). Secondary efficacy parameters also improved in patients treated with Sensipar®. These studies showed that Sensipar® reduced PTH while lowering Ca x P, calcium and phosphorus levels (Table 1, Figure 2). The median dose of Sensipar® at the completion of the studies was 90 mg. Patients with milder disease typically required lower doses.

Similar results were observed when either the iPTH or bio-intact PTH (biPTH) assay was used to measure PTH levels in CKD patients on dialysis; treatment with cinacalcet did not alter the relationship between iPTH and biPTH.

Table 1. Effects of Sensipar® on iPTH, Ca x P, Serum Calcium, and Serum Phosphorus in 6-month Phase 3 Studies (Patients on Dialysis)
 |  | Study 1 |  | Study 2 |  | Study 3
 |  | Placebo (N = 205) | Sensipar® (N = 205) | Placebo (N = 165) | Sensipar® (N = 166) | Placebo (N = 101) | Sensipar® (N = 294)
iPTH
Baseline (pg/mL): | Median; Mean (SD) | 535; 651 (398) | 537; 636 (341) | 556; 630 (317) | 547; 652 (372) | 670; 832 (486) | 703; 848 (685)
Evaluation Phase (pg/mL) |  | 563 | 275 | 592 | 238 | 737 | 339
Median Percent Change |  | +3.8 | -48.3 | +8.4 | -54.1 | +2.3 | -48.2
Patients Achieving Primary Endpoint (iPTH ≤ 250 pg/mL) (%) [iPTH value based on averaging over the evaluation phase (defined as weeks 13 to 26 in studies 1 and 2 and weeks 17 to 26 in study 3) Values shown are medians unless indicated otherwise] |  | 4% | 41% [p < 0.001 compared to placebo; p-values presented for primary endpoint only] | 7% | 46% | 6% | 35%
Patients Achieving ≥ 30% Reduction in iPTH (%) |  | 11% | 61% | 12% | 68% | 10% | 59%
Patients Achieving iPTH ≤ 250 pg/mL and Ca x P < 55 mg^2/dL^2 (%) |  | 1% | 32% | 5% | 35% | 5% | 28%
Ca x P
Baseline (mg^2/dL^2) |  | 62 | 61 | 61 | 61 | 61 | 59
Evaluation Phase (mg^2/dL^2) |  | 59 | 52 | 59 | 47 | 57 | 48
Median Percent Change |  | -2.0 | -14.9 | -3.1 | -19.7 | -4.8 | -15.7
Calcium
Baseline (mg/dL) |  | 9.8 | 9.8 | 9.9 | 10.0 | 9.9 | 9.8
Evaluation Phase (mg/dL) |  | 9.9 | 9.1 | 9.9 | 9.1 | 10.0 | 9.1
Median Percent Change |  | +0.5 | -5.5 | +0.1 | -7.4 | +0.3 | -6.0
Phosphorus
Baseline (mg/dL) |  | 6.3 | 6.1 | 6.1 | 6.0 | 6.1 | 6.0
Evaluation Phase (mg/dL) |  | 6.0 | 5.6 | 5.9 | 5.1 | 5.6 | 5.3
Median Percent Change |  | -1.0 | -9.0 | -2.4 | -12.4 | -5.6 | -8.6

Figure 1. Mean (SE) iPTH Values (Pooled Phase 3 Studies)

Data are presented for patients who completed the studies; Placebo (N = 342), Sensipar® (N = 439).

Figure 2. Mean (SE) Ca x P Values (Pooled Phase 3 Studies)

Data are presented for patients who completed the studies; Placebo (N = 342), Sensipar® (N = 439).

Reductions in iPTH and Ca x P were maintained for up to 12 months of treatment. Sensipar® decreased iPTH and Ca x P levels regardless of disease severity (i.e., baseline iPTH value), duration of dialysis, and whether or not vitamin D sterols were administered. Approximately 60% of patients with mild (iPTH ≥ 300 to ≤ 500 pg/mL), 41% with moderate (iPTH > 500 to 800 pg/mL), and 11% with severe (iPTH > 800 pg/mL) secondary HPT achieved a mean iPTH value of 250 pg/mL. Plasma iPTH levels were measured using the Nichols IRMA.

Parathyroid Carcinoma

Ten patients with parathyroid carcinoma were enrolled in an open-label study. The study consisted of 2 phases, a dose-titration phase and a maintenance phase.

The range of exposure was 2 to 16 weeks in the titration phase (n = 10) and 16 to 48 weeks (n = 3) for the maintenance phase. Baseline mean (SD) serum calcium was 14.7 (1.8) mg/dL. The range of change from baseline to last measurement was –7.5 to 2.7 mg/dL during the titration phase and –7.4 to 0.9 mg/dL during the maintenance phase (Figure 3). No patients maintained a serum calcium level within the normal range. The doses ranged from 70 mg twice daily to 90 mg four times daily for patients in the maintenance phase.

Figure 3. Serum Calcium Values in Parathyroid Carcinoma Patients Receiving Sensipar® at Baseline, Titration and Maintenance Phase

Solid lines represent individual patient data

B = baseline; T = last value in titration phase; M = last value in maintenance phase

Reference lines (dashed) show the normal range for serum calcium values

INDICATIONS AND USAGE

Sensipar® is indicated for the treatment of secondary hyperparathyroidism in patients with Chronic Kidney Disease on dialysis.

Sensipar® is indicated for the treatment of hypercalcemia in patients with parathyroid carcinoma.

CONTRAINDICATIONS

Sensipar® is contraindicated in patients with hypersensitivity to any component(s) of this product.

WARNINGS

Seizures

In three clinical studies of CKD patients on dialysis, 5% of the patients in both the Sensipar® and placebo groups reported a history of seizure disorder at baseline. During the trials, seizures (primarily generalized or tonic-clonic) were observed in 1.4% (9/656) of Sensipar®-treated patients and 0.4% (2/470) of placebo-treated patients. Five of the nine Sensipar®-treated patients had a history of a seizure disorder and two were receiving anti-seizure medication at the time of their seizure. Both placebo-treated patients had a history of seizure disorder and were receiving anti-seizure medication at the time of their seizure. While the basis for the reported difference in seizure rate is not clear, the threshold for seizures is lowered by significant reductions in serum calcium levels. Therefore, serum calcium levels should be closely monitored in patients receiving Sensipar®, particularly in patients with a history of a seizure disorder (see PRECAUTIONS, Hypocalcemia).

Hypotension and/or Worsening Heart Failure

In postmarketing safety surveillance, isolated, idiosyncratic cases of hypotension, worsening heart failure, and/or arrhythmia have been reported in patients with impaired cardiac function, in which a causal relationship to Sensipar® could not be completely excluded and which may be mediated by reductions in serum calcium levels. Clinical trial data showed hypotension occurred in 7% of Sensipar®-treated patients and 12% of placebo-treated patients, heart failure occurred in 2% of both Sensipar®- and placebo-treated patients.

PRECAUTIONS

Hypocalcemia

Sensipar® lowers serum calcium, and therefore patients should be carefully monitored for the occurrence of hypocalcemia. Potential manifestations of hypocalcemia include paresthesias, myalgias, cramping, tetany, and convulsions.

Sensipar® treatment should not be initiated if serum calcium is less than the lower limit of the normal range (8.4 mg/dL). Serum calcium should be measured within 1 week after initiation or dose adjustment of Sensipar®. Once the maintenance dose has been established, serum calcium should be measured approximately monthly (see DOSAGE AND ADMINISTRATION).

If serum calcium falls below 8.4 mg/dL but remains above 7.5 mg/dL, or if symptoms of hypocalcemia occur, calcium-containing phosphate binders and/or vitamin D sterols can be used to raise serum calcium. If serum calcium falls below 7.5 mg/dL, or if symptoms of hypocalcemia persist and the dose of vitamin D cannot be increased, withhold administration of Sensipar® until serum calcium levels reach 8.0 mg/dL, and/or symptoms of hypocalcemia have resolved. Treatment should be re-initiated using the next lowest dose of Sensipar® (see DOSAGE AND ADMINISTRATION).

In the 26-week studies of patients with CKD on dialysis, 66% of patients receiving Sensipar® compared with 25% of patients receiving placebo developed at least one serum calcium value < 8.4 mg/dL. Less than 1% of patients in each group permanently discontinued study drug due to hypocalcemia.

Sensipar® is not indicated for CKD patients not on dialysis. In CKD patients with secondary HPT not on dialysis, the long-term safety and efficacy of Sensipar® have not been established. Clinical studies indicate that Sensipar®-treated CKD patients not on dialysis have an increased risk for hypocalcemia compared to Sensipar®-treated CKD patients on dialysis, which may be due to lower baseline calcium levels. In a phase 3 study of 32 weeks duration and including 404 subjects (302 cinacalcet, 102 placebo), in which the median dose for cinacalcet was 60 mg at the completion of the study, 80% of Sensipar®-treated patients experienced at least one serum calcium value < 8.4 mg/dL compared to 5% of patients receiving placebo.

Adynamic bone disease may develop if iPTH levels are suppressed below 100 pg/mL. One clinical study evaluated bone histomorphometry in patients treated with Sensipar® for one year. Three patients with mild hyperparathyroid bone disease at the beginning of the study developed adynamic bone disease during treatment with Sensipar®. Two of these patients had iPTH levels below 100 pg/mL at multiple time points during the study. In the three 6-month, phase 3 studies conducted in CKD patients on dialysis, 11% of patients treated with Sensipar® had mean iPTH values below 100 pg/mL during the efficacy-assessment phase. If iPTH levels decrease below the NKF-K/DOQI recommended target range (150-300 pg/mL) ^1 in patients treated with Sensipar®, the dose of Sensipar® and/or vitamin D sterols should be reduced or therapy discontinued.

Hepatic Insufficiency

Cinacalcet exposure as assessed by AUC(0-inf) in patients with moderate and severe hepatic impairment (as indicated by the Child-Pugh method) were 2.4 and 4.2 times higher, respectively, than that in normals. Patients with moderate and severe hepatic impairment should be monitored throughout treatment with Sensipar® (see CLINICAL PHARMACOLOGY, Pharmacokinetics and DOSAGE AND ADMINISTRATION).

Information for Patients

It is recommended that Sensipar® be taken with food or shortly after a meal. Tablets should be taken whole and should not be divided.

Patients with CKD on Dialysis with Secondary Hyperparathyroidism

Serum calcium and serum phosphorus should be measured within 1 week and iPTH should be measured 1 to 4 weeks after initiation or dose adjustment of Sensipar®. Once the maintenance dose has been established, serum calcium and serum phosphorus should be measured approximately monthly, and PTH every 1 to 3 months (see DOSAGE AND ADMINISTRATION). All iPTH measurements during the Sensipar® trials were obtained using the Nichols IRMA.

In patients with end-stage renal disease, testosterone levels are often below the normal range. In a placebo-controlled trial in patients with CKD on dialysis, there were reductions in total and free testosterone in male patients following six months of treatment with Sensipar®. Levels of total testosterone decreased by a median of 15.8% in the Sensipar®-treated patients and by 0.6% in the placebo-treated patients. Levels of free testosterone decreased by a median of 31.3% in the Sensipar®-treated patients and by 16.3% in the placebo-treated patients. The clinical significance of these reductions in serum testosterone is unknown.

Patients with Parathyroid Carcinoma

Serum calcium should be measured within 1 week after initiation or dose adjustment of Sensipar®. Once maintenance dose levels have been established, serum calcium should be measured every 2 months (see DOSAGE AND ADMINISTRATION).

Drug Interactions and/or Drug/Laboratory Test Interactions

See CLINICAL PHARMACOLOGY, Pharmacokinetics and Drug Interactions.

Effect of Sensipar® on other drugs:

Drugs metabolized by cytochrome P450 2D6 (CYP2D6): Sensipar® is a strong in vitro, as well as in vivo, inhibitor of CYP2D6. Therefore, dose adjustments of concomitant medications that are predominantly metabolized by CYP2D6 (eg, metoprolol and carvedilol) and particularly those with a narrow therapeutic index (eg, flecainide, vinblastine, thioridazine and most tricyclic antidepressants) may be required.

Desipramine: Concurrent administration of cinacalcet (90 mg) with desipramine (50 mg) increased the exposure of desipramine by 3.6 fold in CYP2D6 extensive metabolizers.

Amitriptyline: Concurrent administration of 25 mg or 100 mg cinacalcet with 50 mg amitriptyline increased amitriptyline exposure and nortriptyline (active metabolite) exposure by approximately 20% in CYP2D6 extensive metabolizers.

Midazolam: There were no significant differences in the pharmacokinetics of midazolam, a CYP3A4 and CYP3A5 substrate, in subjects receiving 90 mg cinacalcet once daily for 5 days and a single dose of 2 mg midazolam on day 5 as compared to those of subjects receiving 2 mg midazolam alone. This suggests that cinacalcet would not affect the pharmacokinetics of drugs predominantly metabolized by CYP3A4 and CYP3A5.

Effect of other drugs on Sensipar®:

Sensipar® is metabolized by multiple cytochrome P450 enzymes, primarily CYP3A4, CYP2D6, and CYP1A2.

Ketoconazole: Sensipar® is metabolized in part by CYP3A4. Co-administration of ketoconazole, a strong inhibitor of CYP3A4, increased cinacalcet exposure following a single 90 mg dose of Sensipar® by 2.3 fold. Dose adjustment of Sensipar® may be required and PTH and serum calcium concentrations should be closely monitored if a patient initiates or discontinues therapy with a strong CYP3A4 inhibitor (e.g., ketoconazole, erythromycin, itraconazole; see DOSAGE AND ADMINISTRATION).

Carcinogenesis, Mutagenesis, and Impairment of Fertility

Carcinogenicity: Standard lifetime dietary carcinogenicity bioassays were conducted in mice and rats. Mice were given dietary doses of 15, 50, 125 mg/kg/day in males and 30, 70, 200 mg/kg/day in females (exposures up to 2 times those resulting with a human oral dose of 180 mg/day based on AUC comparison). Rats were given dietary doses of 5, 15, 35 mg/kg/day in males and 5, 20, 35 mg/kg/day in females (exposures up to 2 times those resulting with a human oral dose of 180 mg/day based on AUC comparison). No increased incidence of tumors was observed following treatment with cinacalcet.

Mutagenicity: Cinacalcet was not genotoxic in the Ames bacterial mutagenicity assay or in the Chinese Hamster Ovary (CHO) cell HGPRT forward mutation assay and CHO cell chromosomal aberration assay, with and without metabolic activation or in the in vivo mouse micronucleus assay.

Impairment of Fertility: Female rats were given oral gavage doses of 5, 25, 75 mg/kg/day beginning 2 weeks before mating and continuing through gestation day 7. Male rats were given oral doses 4 weeks prior to mating, during mating (3 weeks) and 2 weeks post-mating. No effects were observed in male or female fertility at 5 and 25 mg/kg/day (exposures up to 3 times those resulting with a human oral dose of 180 mg/day based on AUC comparison). At 75 mg/kg/day, there were slight adverse effects (slight decreases in body weight and food consumption) in males and females.

Pregnancy Category C

In pregnant female rats given oral gavage doses of 2, 25, 50 mg/kg/day during gestation no teratogenicity was observed at doses up to 50 mg/kg/day (exposure 4 times those resulting with a human oral dose of 180 mg/day based on AUC comparison). Decreased fetal body weights were observed at all doses (less than 1 to 4 times a human oral dose of 180 mg/day based on AUC comparison) in conjunction with maternal toxicity (decreased food consumption and body weight gain).

In pregnant female rabbits given oral gavage doses of 2, 12, 25 mg/kg/day during gestation no adverse fetal effects were observed (exposures less than with a human oral dose of 180 mg/day based on AUC comparisons). Reductions in maternal food consumption and body weight gain were seen at doses of 12 and 25 mg/kg/day.

In pregnant rats given oral gavage doses of 5, 15, 25 mg/kg/day during gestation through lactation no adverse fetal or pup (post-weaning) effects were observed at 5 mg/kg/day (exposures less than with a human therapeutic dose of 180 mg/day based on AUC comparisons). Higher doses of 15 and 25 mg/kg/day (exposures 2-3 times a human oral dose of 180 mg/day based on AUC comparisons) were accompanied by maternal signs of hypocalcemia (periparturient mortality and early postnatal pup loss), and reductions in postnatal maternal and pup body-weight gain. Sensipar® has been shown to cross the placental barrier in rabbits.

There are no adequate and well-controlled studies in pregnant women. Sensipar® should be used during pregnancy only if the potential benefit justifies the potential risk to the fetus.

Lactating Women

Studies in rats have shown that Sensipar® is excreted in the milk with a high milk-to-plasma ratio. It is not known whether this drug is excreted in human milk. Considering these data in rats and because many drugs are excreted in human milk and because of the potential for clinically significant adverse reactions in infants from Sensipar®, a decision should be made whether to discontinue nursing or to discontinue the drug, taking into account the importance of the drug to the lactating woman.

Pediatric Use

The safety and efficacy of Sensipar® in pediatric patients have not been established.

Geriatric Use

Of the 1136 patients enrolled in the Sensipar® phase 3 clinical program, 26% were ≥ 65 years old, and 9% were ≥ 75 years old. No differences in the safety and efficacy of Sensipar® were observed in patients greater or less than 65 years of age (see DOSAGE AND ADMINISTRATION, Geriatric patients).

ADVERSE EVENTS

Secondary Hyperparathyroidism in Patients with Chronic Kidney Disease on Dialysis

In 3 double-blind placebo-controlled clinical trials, 1126 CKD patients on dialysis received study drug (656 Sensipar®, 470 placebo) for up to 6 months. The most frequently reported adverse events (incidence of at least 5% in the Sensipar® group and greater than placebo) are provided in Table 2. The most frequently reported events in the Sensipar® group were nausea, vomiting, and diarrhea.

Table 2. Adverse Event Incidence (≥ 5%) in Patients on Dialysis
Event [Included are events that were reported at a greater incidence in the Sensipar® group than in the placebo group.] : | Placebo (n = 470) (%) | Sensipar® (n = 656) (%)
Nausea | 19 | 31
Vomiting | 15 | 27
Diarrhea | 20 | 21
Myalgia | 14 | 15
Dizziness | 8 | 10
Hypertension | 5 | 7
Asthenia | 4 | 7
Anorexia | 4 | 6
Pain Chest, NonCardiac | 4 | 6
Access Infection | 4 | 5

The incidence of serious adverse events (29% vs. 31%) was similar in the Sensipar® and placebo groups, respectively.

12-Month Experience with Sensipar®: Two hundred and sixty-six patients from 2 phase 3 studies continued to receive Sensipar® or placebo treatment in a 6-month double-blind extension study (12-month total treatment duration). The incidence and nature of adverse events in this study were similar in the two treatment groups, and comparable to those observed in the phase 3 studies.

Postmarketing Experience with Sensipar®: Rash, hypersensitivity reactions (including angioedema and urticaria), diarrhea and myalgia have been identified as adverse reactions during post-approval use of Sensipar®. Isolated, idiosyncratic cases of hypotension, worsening heart failure, and/ or arrhythmia have been reported in Sensipar®-treated patients with impaired cardiac function in postmarketing safety surveillance. Because these reactions are reported voluntarily from a population of uncertain size, it is not always possible to reliably estimate their frequency or establish a causal relationship to drug exposure.

Parathyroid Carcinoma

The most frequent adverse events in this patient group were nausea and vomiting.

Laboratory values: Serum calcium levels should be closely monitored in patients receiving Sensipar® (see PRECAUTIONS and DOSAGE AND ADMINISTRATION).

OVERDOSAGE

Doses titrated up to 300 mg once daily have been safely administered to patients on dialysis. Overdosage of Sensipar® may lead to hypocalcemia. In the event of overdosage, patients should be monitored for signs and symptoms of hypocalcemia and appropriate measures taken to correct serum calcium levels (see PRECAUTIONS).

Since Sensipar® is highly protein bound, hemodialysis is not an effective treatment for overdosage of Sensipar®.

DOSAGE AND ADMINISTRATION

Sensipar® tablets should be taken whole and should not be divided. Sensipar® should be taken with food or shortly after a meal.

Dosage must be individualized.

Secondary Hyperparathyroidism in Patients with Chronic Kidney Disease on Dialysis

The recommended starting oral dose of Sensipar® is 30 mg once daily. Serum calcium and serum phosphorus should be measured within 1 week and PTH should be measured 1 to 4 weeks after initiation or dose adjustment of Sensipar®. Sensipar® should be titrated no more frequently than every 2 to 4 weeks through sequential doses of 60, 90, 120, and 180 mg once daily to target iPTH consistent with the NKF-K/DOQI recommendation for CKD patients on dialysis of 150-300 pg/mL. PTH levels should be assessed no earlier than 12 hours after dosing with Sensipar®.

Sensipar® can be used alone or in combination with vitamin D sterols and/or phosphate binders.

During dose titration, serum calcium levels should be monitored frequently and if levels decrease below the normal range, appropriate steps should be taken to increase serum calcium levels, such as by providing supplemental calcium, initiating or increasing the dose of calcium-based phosphate binder, initiating or increasing the dose of vitamin D sterols, or temporarily withholding treatment with Sensipar® (see PRECAUTIONS).

Parathyroid Carcinoma

The recommended starting oral dose of Sensipar® is 30 mg twice daily.

The dosage of Sensipar® should be titrated every 2 to 4 weeks through sequential doses of 30 mg twice daily, 60 mg twice daily, 90 mg twice daily, and 90 mg three or four times daily as necessary to normalize serum calcium levels.

Special Populations

Geriatric patients: Age does not alter the pharmacokinetics of Sensipar®; no dosage adjustment is required for geriatric patients.

Patients with renal impairment: Renal impairment does not alter the pharmacokinetics of Sensipar®; no dosage adjustment is necessary for renal impairment.

Patients with hepatic impairment: Cinacalcet exposures, as assessed by AUC(0-inf), in patients with moderate and severe hepatic impairment (as indicated by the Child-Pugh method) were 2.4 and 4.2 times higher, respectively, than in normals. In patients with moderate and severe hepatic impairment, PTH and serum calcium concentrations should be closely monitored throughout treatment with Sensipar® (see CLINICAL PHARMACOLOGY, Pharmacokinetics and PRECAUTIONS).

Drug Interactions

Sensipar® is metabolized in part by the enzyme CYP3A4. Co-administration of ketoconazole, a strong inhibitor of CYP3A4, caused an approximate 2-fold increase in cinacalcet exposure. Dose adjustment of Sensipar® may be required and PTH and serum calcium concentrations should be closely monitored if a patient initiates or discontinues therapy with a strong CYP3A4 inhibitor (e.g., ketoconazole, erythromycin, itraconazole; see CLINICAL PHARMACOLOGY, Pharmacokinetics and PRECAUTIONS).

HOW SUPPLIED

Sensipar® 30 mg tablets are formulated as light-green, film-coated, oval-shaped tablets marked with “AMG” on one side and “30” on the opposite side.

Sensipar® 60 mg tablets are formulated as light-green, film-coated, oval-shaped tablets marked with “AMG” on one side and “60” on the opposite side.

Sensipar® 90 mg tablets are formulated as light-green, film-coated, oval-shaped tablets marked with “AMG” on one side and “90” on the opposite side.

They are supplied by State of Florida DOH Central Pharmacy as follows:

NDC | Strength | Quantity/Form | Color | Source Prod. Code
53808-0577-1 | 30 mg | 30 Tablets in a Blister Pack | light green | 55513-073
53808-0578-1 | 60 mg | 30 Tablets in a Blister Pack | light green | 55513-074

Storage

Store at 25ºC (77ºF); excursions permitted to 15-30ºC (59-86ºF). [See USP controlled room temperature].

Rx Only

This product, or its use, may be covered by one or more US Patents including US Patent Nos. 6313146, 6211244, 6031003 and 6011068, in addition to others, including patents pending.

REFERENCES

1. National Kidney Foundation: K/DOQI clinical practice guidelines: bone metabolism and disease in chronic kidney disease. American Journal of Kidney Disease 4 2:S1-S201, 2003

Manufactured for: Amgen
Amgen Inc.
One Amgen Center Drive
Thousand Oaks, CA 91320-1799

©2004-2010 Amgen Inc. All rights reserved.

This Product was Repackaged By:

State of Florida DOH Central Pharmacy
104-2 Hamilton Park Drive
Tallahassee, FL 32304
United States

PACKAGE LABEL - PRINCIPAL DISPLAY PANEL - TABLET, 30 MG

Amgen®

NDC 53808-0577-1

Sensipar®

(cinacalcet HCI) Tablets

Rx Only

30 tablets

30 mg

Store at 25°C (77°F); excursions permitted to 15-30°C (59-86°F).

See USP controlled room temperature.

PACKAGE LABEL - PRINCIPAL DISPLAY PANEL - TABLET, 60 MG

Amgen®

NDC 53808-0578-1

Sensipar®

(cinacalcet HCI) Tablets

Rx Only

30 tablets

60 mg

Store at 25°C (77°F); excursions permitted to 15-30°C (59-86°F).

See USP controlled room temperature.